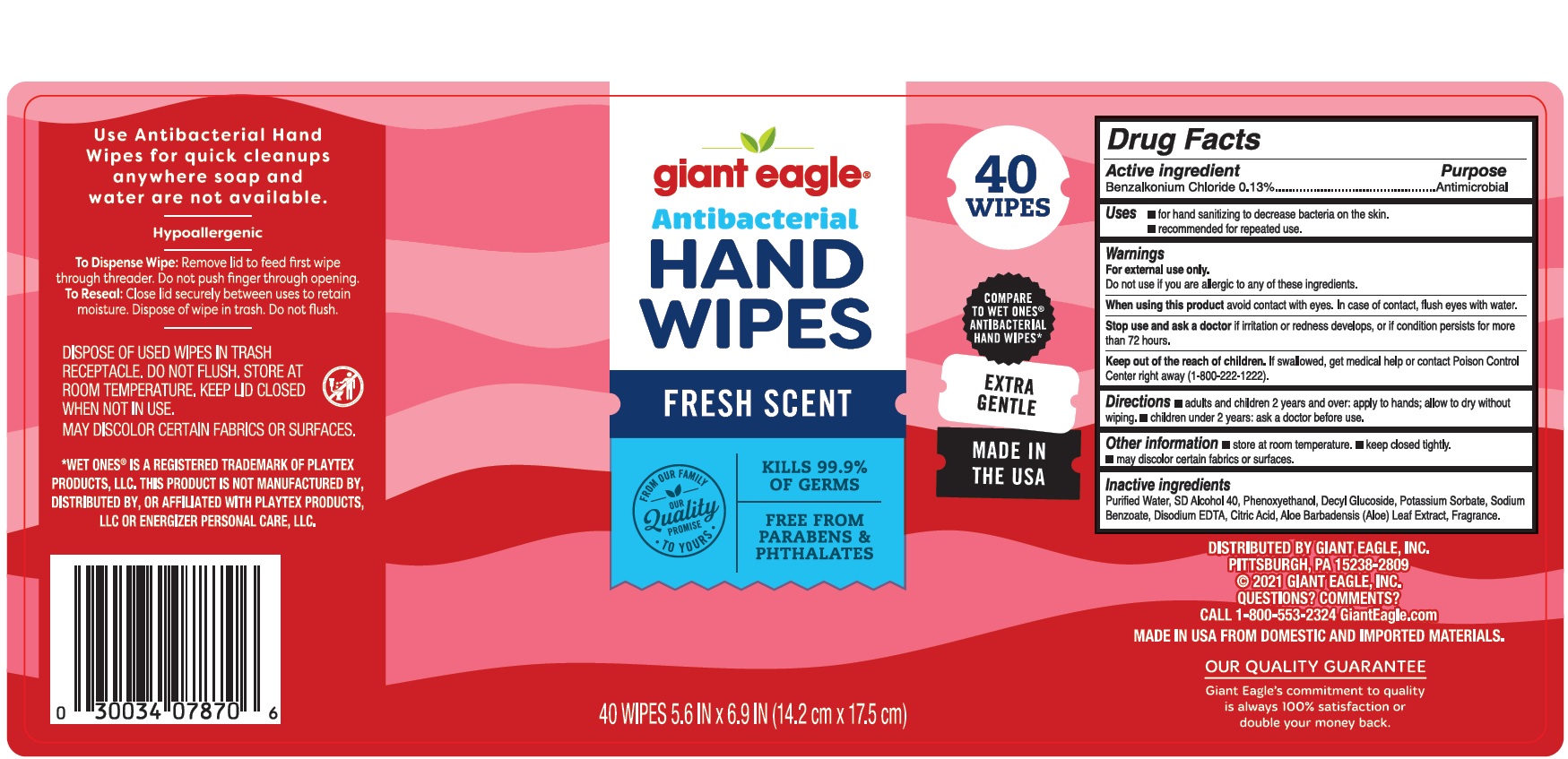 DRUG LABEL: Giant Eagle Antibacterial Hand Wipes
NDC: 56194-575 | Form: CLOTH
Manufacturer: Giant Eagle
Category: otc | Type: HUMAN OTC DRUG LABEL
Date: 20251205

ACTIVE INGREDIENTS: BENZALKONIUM CHLORIDE 0.13 g/100 1
INACTIVE INGREDIENTS: DECYL GLUCOSIDE; POTASSIUM SORBATE; WATER; EDETATE DISODIUM ANHYDROUS; SODIUM BENZOATE; PHENOXYETHANOL; CITRIC ACID MONOHYDRATE; ALOE VERA LEAF; ALCOHOL

Giant Eagle Drug Facts

Active ingredient

Benzalkonium Chloride 0.13%

Purpose

Antimicrobial

Uses

- for hand sanitizing to decrease bacteria on the skin.
- recommended for repeated use

Warnings

For external use only.

When using this product

avoid contact with eyes. In case of contact, flush eyes with water.

Stop use and ask a doctor

if irritation or redness develops, or if condition persists for more than 72 hours.

Keep out of the reach of children.

If swallowed, get medical help or contact Poison Control Center right away (1-800-222-1222)

Directions

- adults and children 2 years and over: apply to hands; allow to dry without wiping.
- children under 2 years: ask a doctor before use.

Other information

- store at room temperature
- keep closed tightly.
- may discolor certain fabrics or surfaces

Inactive ingredients

Purified Waterr, SD Alcohol 40, Phenoxyethanol, Decyl Glucoside, Potassium Sorbate, Sodium Benzoate, Disodium EDTA, Citric Acid, Aloe Barbadensis (Aloe) Leaf Extract, Fragrance.

Principal Display Panel

giant eagle

Antibacterial

HAND

WIPES

FRESH SCENT

40 WIPES